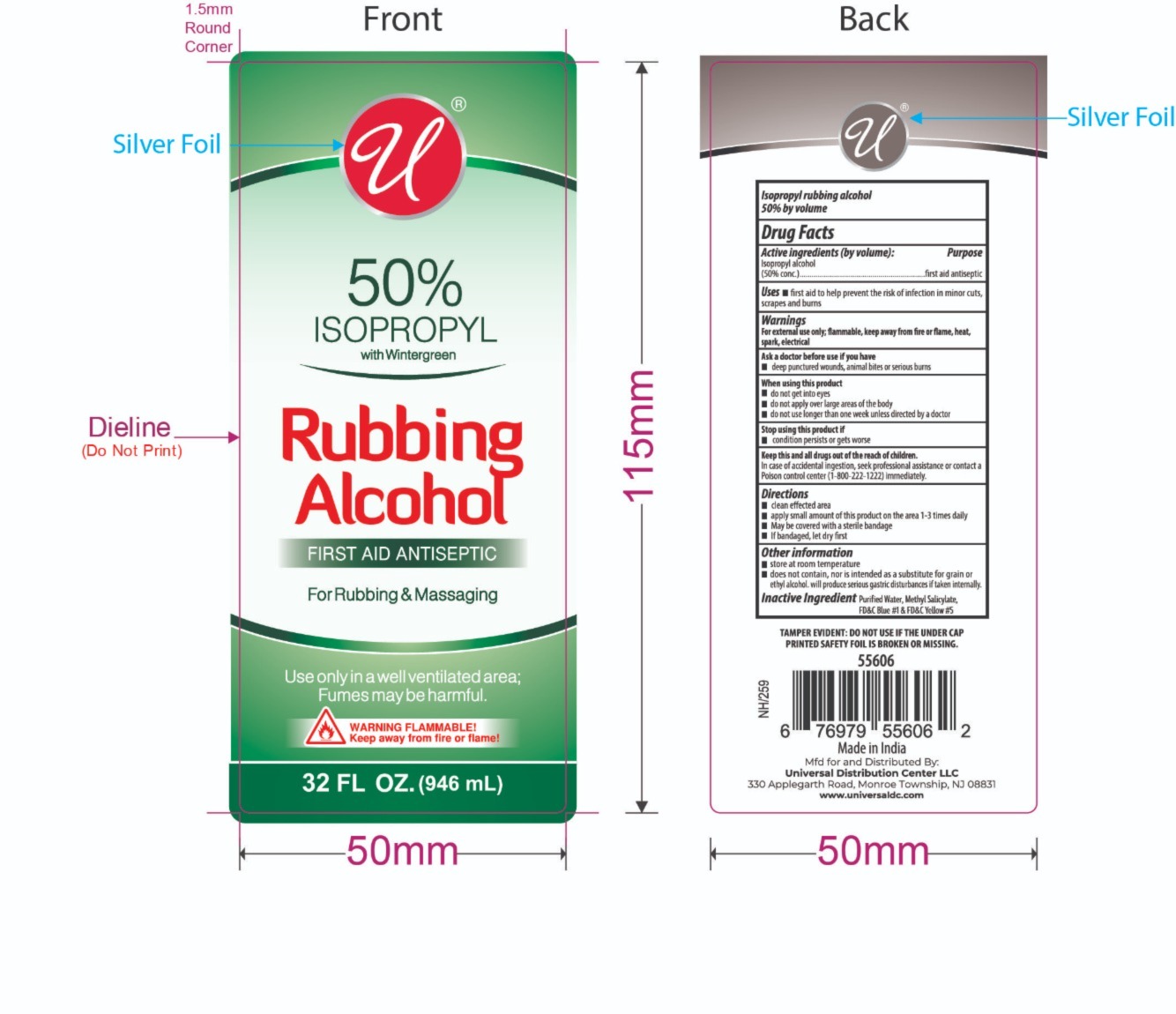 DRUG LABEL: ISOPROPYL RUBBING ALCOHOL 50% WITH WINTERGREEN
NDC: 52000-802 | Form: LIQUID
Manufacturer: Universal Distribution Center LLC
Category: otc | Type: HUMAN OTC DRUG LABEL
Date: 20250305

ACTIVE INGREDIENTS: ISOPROPYL ALCOHOL 50 mL/100 mL
INACTIVE INGREDIENTS: WATER; METHYL SALICYLATE; PEG-75 LANOLIN; FD&C BLUE NO. 1; FD&C YELLOW NO. 5

ISOPROPYL RUBBING ALCOHOL 50% WITH WINTERGREEN

Active ingredient (by volume)

Isopropyl alcohol (50% concentrate)

Purpose

topical antimicrobial

Uses

- to decrease germs in minor cuts and scrapes
- helps relieve minor muscular aches due to exertion

Warnings

For external use only

- flammable, keep away from fire and flame
- will produce serious gastric disturbances if taken internally

Ask a doctor before use if you havedeep puncture wounds or serious burns

When using this product

- do not get into eyes or mucous membranes
- use only in a well-ventilated area

Stop use and ask a doctor ifcondition persists or gets worse

Keep out of reach of children.

In case of an accidental ingestion, contact a Poison Control Center immediately

Directions

- apply to skin directly of with clean gauze, cotton or swab
- for rubbing apply liberally and rub with hands

Other information

- does not contain, nor is intended as a substitute for grain or ethyl alcohol
- keep bottle tightly closed

Inactive ingredient

Water, methyl salicylate, laneth-75, FD&C Blue #1, FD&C Yellow #5

PRINCIPAL DISPLAY PANEL

HEALTH SMART ISOPROPYL RUBBING ALCOHOL 50% WITH WINTERGREEN

TOPICAL ANTIMICROBIAL

12 FL.OZ (354 mL)